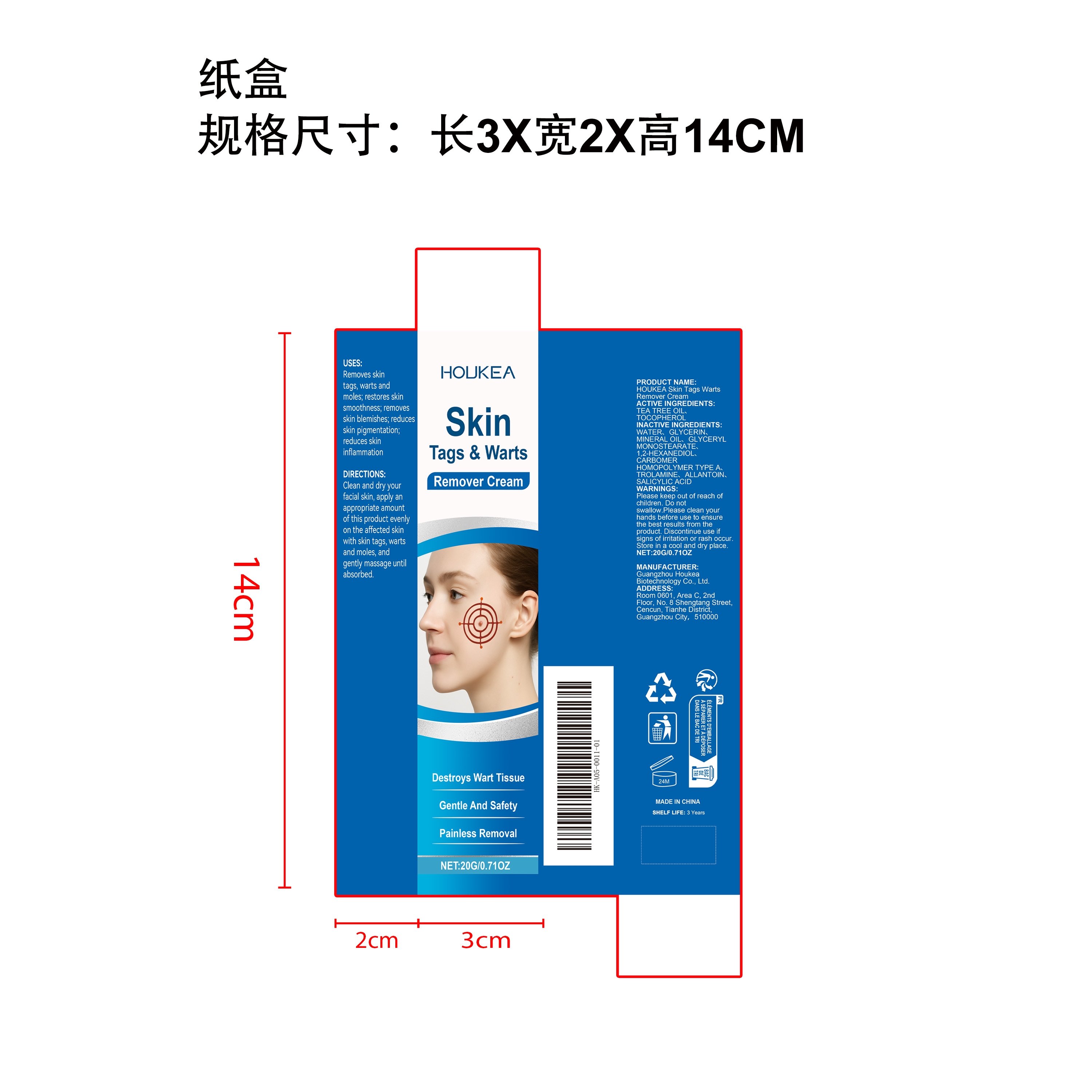 DRUG LABEL: HOUKEA Skin Tags Warts Remover Cream
NDC: 84984-007 | Form: CREAM
Manufacturer: Guangzhou Houkea Biotechnology Co., Ltd.
Category: otc | Type: HUMAN OTC DRUG LABEL
Date: 20251127

ACTIVE INGREDIENTS: TEA TREE OIL 0.004 mg/20 mg
INACTIVE INGREDIENTS: TOCOPHEROL 0.004 mg/20 mg; WATER 17.204 mg/20 mg; SALICYLIC ACID 0.004 mg/20 mg; TROLAMINE 0.04 mg/20 mg; MINERAL OIL 0.6 mg/20 mg; CARBOMER HOMOPOLYMER TYPE A 0.04 mg/20 mg; GLYCERYL MONOSTEARATE 0.4 mg/20 mg; 1,2-HEXANEDIOL 0.1 mg/20 mg; ALLANTOIN 0.004 mg/20 mg; GLYCERIN 1.6 mg/20 mg

ACTIVE INGREDIENT

TEA TREE OIL

PURPOSE

Removes skin tags, warts and moles；restores skin smoothness;；removes skin blemishes；reduces skin pigmentation；reduces skin inflammation

WHEN USING

Clean and dry your facial skin, apply an appropriate amount of this product evenly on the affected skin with skin tags, warts and moles, and gently massage until absorbed.

WARNINGS

Please keep out of reach of children. Do not swallow.Please clean your hands before use to ensure the best results from the product. Discontinue use if signs of irritation or rash occur. Store in a cool and dry place.

DO NOT USE

Discontinue use if signs of irritation or rash occur.

STOP USE

Discontinue use if signs of irritation or rash occur.

KEEP OUT OF REACH OF CHILDREN

Please keep out of reach of children. Do not swallow.

STORAGE AND HANDLING

Store in a cool and dry place.

INACTIVE INGREDIENT

TOCOPHEROL、WATER、GLYCERIN、 MINERAL OIL、 GLYCERYL MONOSTEARATE、 1,2-HEXANEDIOL、 CARBOMER HOMOPOLYMER TYPE A TROLAMINE、 ALLANTOIN、 SALICYLIC ACID

DOSAGE AND ADMINISTRATION

Clean and dry your facial skin, apply an appropriate amount of this product evenly on the affected skin with skin tags, warts and moles, and gently massage until absorbed.

INDICATIONS AND USAGE

Clean and dry your facial skin, apply an appropriate amount of this product evenly on the affected skin with skin tags, warts and moles, and gently massage until absorbed.